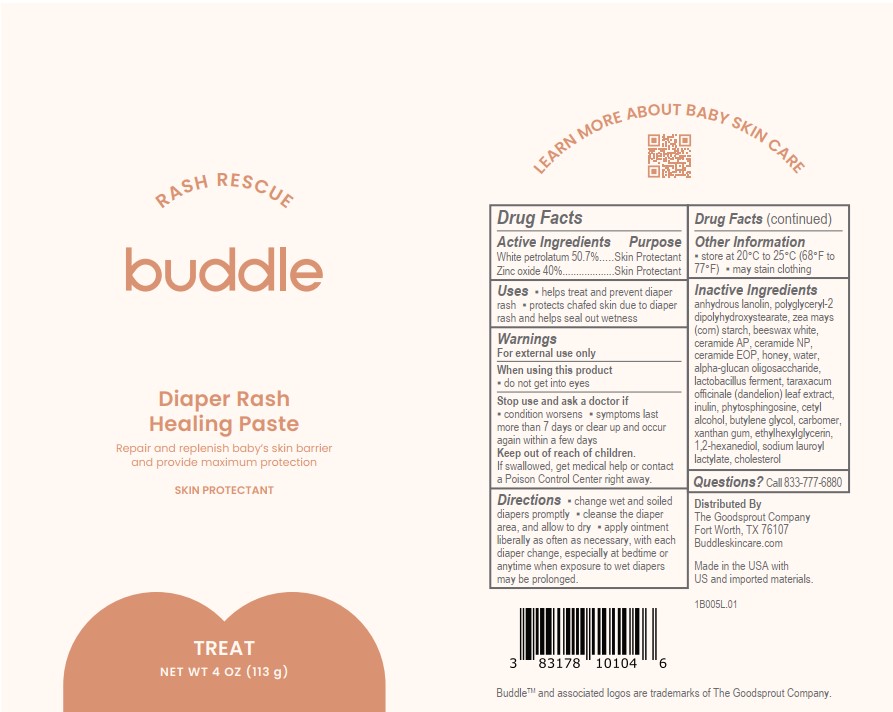 DRUG LABEL: Buddle Diaper Rash Rescue Healing
NDC: 83178-101 | Form: PASTE
Manufacturer: The Goodsprout Company LLC
Category: otc | Type: HUMAN OTC DRUG LABEL
Date: 20241223

ACTIVE INGREDIENTS: WHITE PETROLATUM 50.7 g/100 g; ZINC OXIDE 40 g/100 g
INACTIVE INGREDIENTS: HONEY; WATER; CARBOMER HOMOPOLYMER, UNSPECIFIED TYPE; ETHYLHEXYLGLYCERIN; WHITE WAX; CERAMIDE NP; POLYGLYCERYL-2 DIPOLYHYDROXYSTEARATE; BUTYLENE GLYCOL; STARCH, CORN; INULIN; TARAXACUM OFFICINALE LEAF; .ALPHA.-GLUCAN OLIGOSACCHARIDE; CHOLESTEROL; 1,2-HEXANEDIOL; CERAMIDE AP; PHYTOSPHINGOSINE; LIMOSILACTOBACILLUS FERMENTUM; SODIUM LAUROYL LACTYLATE; CERAMIDE 1; LANOLIN; CETYL ALCOHOL; XANTHAN GUM

Active Ingredients

White petrolatum 50.7%

Zinc oxide 40%

Purposes

White petrolatum 50.7% ...... Skin Protectant

Zinc oxide 40% .................... Skin Protectant

Uses

- helps treat and prevent diaper rash
- protects chafed skin due to diaper rash and helps seal out wetness

Warnings

For external use only

When using this product

- do not get into eyes

Stop use and ask a doctor if

- condition worsens
- symptoms last more than 7 days or clear up and occur again within a few days

Keep out of reach of children.

If swallowed, get medical help or contact a Poison Control Center right away.

Directions

- change wet and soiled diapers promptly
- cleanse the diaper area, and allow to dry
- apply ointment liberally as often as necessary, with each diaper change, especially at bedtime or anytime when exposure to wet diapers may be prolonged.

Other Information

- store at 20°C to 25°C (68°F to 77°F)
- may stain clothing

Inactive Ingredients

anhydrous lanolin, polyglyceryl-2 dipolyhydroxystearate, zea mays (corn) starch, beeswax white, ceramide AP, ceramide NP, ceramide EOP, honey, water, alpha-glucan oligosaccharide, lactobacillus ferment, taraxacum officinale (dandelion) leaf extract, inulin, phytosphingosine, cetyI alcohol, butylene glycol, carbomer, xanthan gum, ethylhexylglycerin, 1,2-hexanediol, sodium lauroyl lactylate, cholesterol

Questions?

Call 833-777-6880

PACKAGE LABEL

RASH RESCUE

buddle

Diaper Rash

Healing Paste

Repair and replenish baby’s skin barrier and provide maximum protection

SKIN PROTECTANT
TREAT

NET WT 4 OZ (113g)